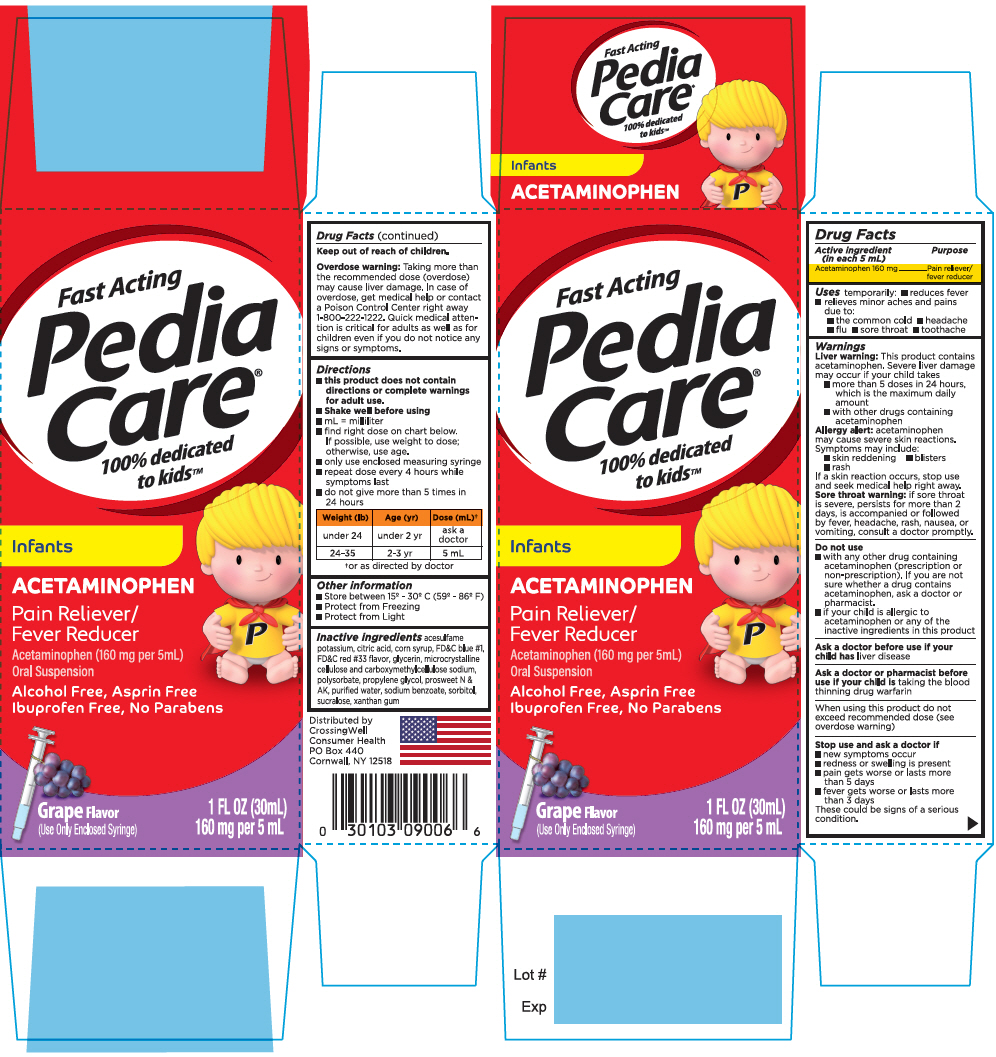 DRUG LABEL: Pediacare Childrens Acetaminophen Grape
NDC: 52412-906 | Form: SUSPENSION
Manufacturer: RANDOB LABS,LTD. DBA CROSSINGWELL CONSUMER HEALTH
Category: otc | Type: HUMAN OTC DRUG LABEL
Date: 20241230

ACTIVE INGREDIENTS: ACETAMINOPHEN 160 mg/5 mL
INACTIVE INGREDIENTS: ACESULFAME POTASSIUM; CITRIC ACID MONOHYDRATE; CORN SYRUP; FD&C BLUE NO. 1; D&C RED NO. 33; GLYCERIN; MICROCRYSTALLINE CELLULOSE; POLYSORBATE 60; PROPYLENE GLYCOL; WATER; SODIUM BENZOATE; SORBITOL; SUCRALOSE; XANTHAN GUM

Pediacare®Children's Acetaminophen Grape

Drug Facts

Active ingredient (in each 5 mL)

Acetaminophen 160 mg

Purpose

Pain reliever/fever reducer

Uses

temporarily:

- reduces fever
- relieves minor aches and pains due to:
  - the common cold
  - headache
  - flu
  - sore throat
  - toothache

Warnings

Liver warning

This product contains acetaminophen. Severe liver damage may occur if your child takes

- more than 5 doses in 24 hours, which is the maximum daily amount
- with other drugs containing acetaminophen

Allergy alert:acetaminophen may cause severe skin reactions. Symptoms may include:

- skin reddening
- blisters
- rash

If a skin reaction occurs, stop use and seek medical help right away.

Sore throat warning:if sore throat is severe, persists for more than 2 days, is accompanied or followed by fever, headache, rash, nausea, or vomiting, consult a doctor promptly.

Do not use

- with any other drug containing acetaminophen (prescription or non-prescription). If you are not sure whether a drug contains acetaminophen, ask a doctor or pharmacist.
- if your child is allergic to acetaminophen or any of the inactive ingredients in this product

Ask a doctor before use if your child hasliver disease

Ask a doctor or pharmacist before use if your child istaking the blood thinning drug warfarin

When using this product do not exceed recommended dose (see overdose warning)

Stop use and ask a doctor if

- new symptoms occur
- redness or swelling is present
- pain gets worse or lasts more than 5 days
- fever gets worse or lasts more than 3 days

These could be signs of a serious condition.

Keep out of reach of children.

Overdose warning

Taking more than the recommended dose (overdose) may cause liver damage. In case of overdose, get medical help or contact a Poison Control Center right away 1-800-222-1222. Quick medical attention is critical for adults as well as for children even if you do not notice any signs or symptoms.

Directions

- this product does not contain directions or complete warnings for adult use.
- Shake well before using
- mL = milliliter
- find right dose on chart below. If possible, use weight to dose; otherwise, use age.
- only use enclosed measuring syringe
- repeat dose every 4 hours while symptoms last
- do not give more than 5 times in 24 hours

Weight (lb) | Age (yr) | Dose (mL) [or as directed by doctor]
under 24 | under 2 yr | ask a doctor
24-35 | 2-3 yr | 5 mL

Other information

- Store between 15° - 30° C (59° - 86° F)
- Protect from Freezing
- Protect from Light

Inactive ingredients

acesulfame potassium, citric acid, corn syrup, FD&C blue #1, FD&C red #33 flavor, glycerin, microcrystalline cellulose and carboxymethylcellulose sodium, polysorbate, propylene glycol, prosweet N & AK, purified water, sodium benzoate, sorbitol, sucralose, xanthan gum

Distributed by
CrossingWell
Consumer Health
PO Box 440
Cornwall, NY 12518

PRINCIPAL DISPLAY PANEL - 30 mL Bottle Carton

Fast Acting
Pedia
Care®
100% dedicated
to kids™

Infants

ACETAMINOPHEN

Pain Reliever/
Fever Reducer

Acetaminophen (160 mg per 5mL)
Oral Suspension

Alcohol Free, Asprin Free
Ibuprofen Free, No Parabens

Grape Flavor
(Use Only Enclosed Syringe)

1 FL OZ (30mL)
160 mg per 5 mL